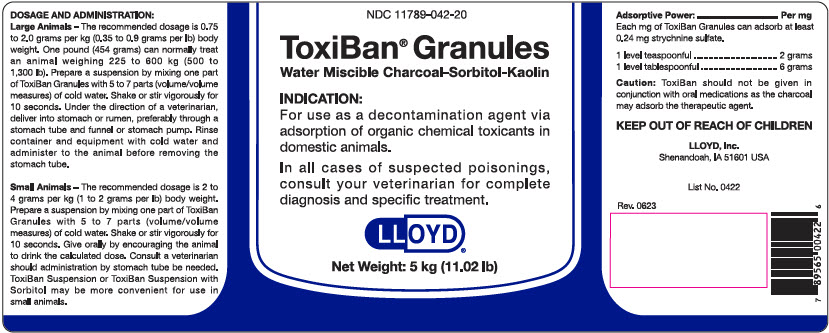 DRUG LABEL: ToxiBan
NDC: 11789-042 | Form: GRANULE
Manufacturer: LLOYD, Inc. of Iowa
Category: animal | Type: OTC ANIMAL DRUG LABEL
Date: 20230711

ACTIVE INGREDIENTS: ACTIVATED CHARCOAL 240 [arb'U]/1 g
INACTIVE INGREDIENTS: KAOLIN; SORBITOL

ToxiBan®

VETERINARY INDICATIONS

INDICATION:

For use as a decontamination agent via adsorption of organic chemical toxicants in domestic animals.

In all cases of suspected poisonings, consult your veterinarian for complete diagnosis and specific treatment.

DOSAGE AND ADMINISTRATION:

Large Animals – The recommended dosage is 0.75 to 2.0 grams per kg (0.35 to 0.9 grams per lb) body weight. One pound (454 grams) can normally treat an animal weighing 225 to 600 kg (500 to 1,300 lb). Prepare a suspension by mixing one part of ToxiBan Granules with 5 to 7 parts (volume/volume measures) of cold water. Shake or stir vigorously for 10 seconds. Under the direction of a veterinarian, deliver into stomach or rumen, preferably through a stomach tube and funnel or stomach pump. Rinse container and equipment with cold water and administer to the animal before removing the stomach tube.

Small Animals – The recommended dosage is 2 to 4 grams per kg (1 to 2 grams per lb) body weight. Prepare a suspension by mixing one part of ToxiBan Granules with 5 to 7 parts (volume/volume measures) of cold water. Shake or stir vigorously for 10 seconds. Give orally by encouraging the animal to drink the calculated dose. Consult a veterinarian should administration by stomach tube be needed. ToxiBan Suspension or ToxiBan Suspension with Sorbitol may be more convenient for use in small animals.

Adsorptive Power: ................................. Per mg

Each mg of ToxiBan Granules can adsorb at least 0.24 mg strychnine sulfate.

STORAGE AND HANDLING

1 level teaspoonful .................................. 2 grams

1 level tablespoonful ............................... 6 grams

PRECAUTIONS

Caution: ToxiBan should not be given in conjunction with oral medications as the charcoal may adsorb the therapeutic agent.

KEEP OUT OF REACH OF CHILDREN

LLOYD, Inc.
Shenandoah, IA 51601 USA

List No. 0422

Rev. 0623

PRINCIPAL DISPLAY PANEL - 5 kg Pail Label

NDC 11789-042-20

ToxiBan® Granules
Water Miscible Charcoal-Sorbitol-Kaolin

INDICATION:

For use as a decontamination agent via
adsorption of organic chemical toxicants in
domestic animals.

In all cases of suspected poisonings,
consult your veterinarian for complete
diagnosis and specific treatment.

LLOYD®

Net Weight: 5 kg (11.02 lb)